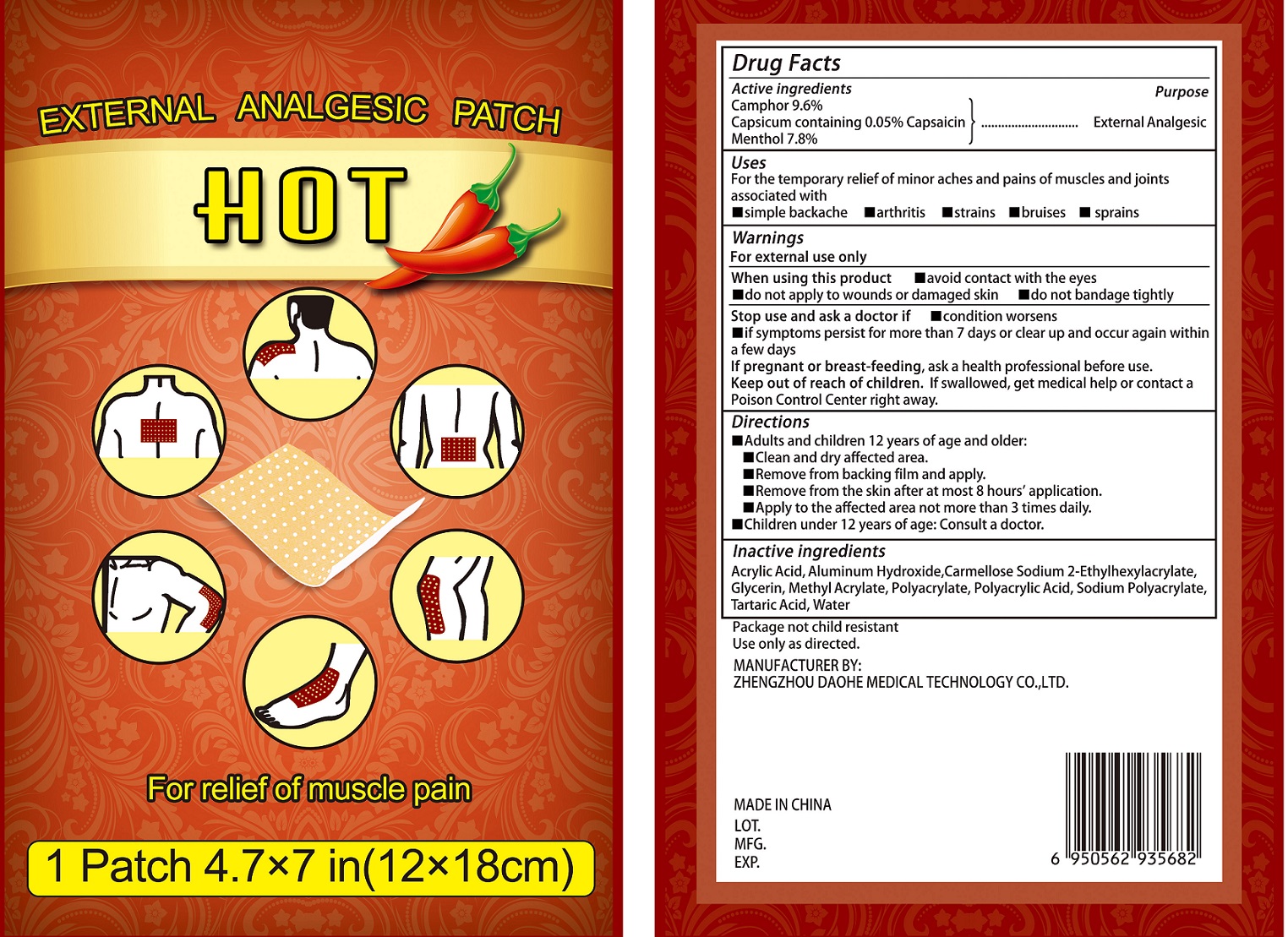 DRUG LABEL: EXTERNAL ANALGESIC
NDC: 73567-001 | Form: PATCH
Manufacturer: Zhengzhou Daohe Medical Technology Co.,Ltd
Category: otc | Type: HUMAN OTC DRUG LABEL
Date: 20231226

ACTIVE INGREDIENTS: CAMPHOR (SYNTHETIC) 96 mg/1 mL; CAPSICUM 0.5 mg/1 mL; MENTHOL 78 mg/1 mL
INACTIVE INGREDIENTS: ACRYLIC ACID; ALUMINUM HYDROXIDE; GLYCERIN; METHYL ACRYLATE; TARTARIC ACID; WATER

EXTERNAL ANALGESIC PATCH

Active ingredients

Camphor 9.6%

Capsicum containing 0.05% Capsaicin

Menthol 7.8%

Purpose

External Analgesic

Uses

For the temporary relief of minor aches and pains of muscles and joints associated with

- simple backache
- arthritis
- strains
- bruises
- sprains

Warnings

For external use only

When using this product

- avoid contact with the eyes
- do not apply to wounds or damaged skin
- do not bandage tightly

Stop use and ask a doctor if

- condition worsens
- if symptoms persist for more than 7 days or clear up and occur again within a few days

If pregnant or breast-feeding,

ask a health professional before use.

Keep out of reach of children.

If swallowed, get medical help or contact a Poison Control Center right away.

Directions

- Adults and children 12 years of age and older:
- Clean and dry affected area.
- Remove from backing film and apply.
- Remove from the skin after at most 8 hour's application
- Apply to the affected area not more than 3 times daily.
- Children under 12 years of age: Consult a doctor.

Inactive ingredients

Acrylic Acid, Aluminum Hydroxide, Carmellose Sodium 2-Ethylhexylacrylate, Glycerin, Methyl Acrylate, Polyacrylate, Polyacrylic Acid, Sodium Polyacrylate, Tartaric Acid, Water